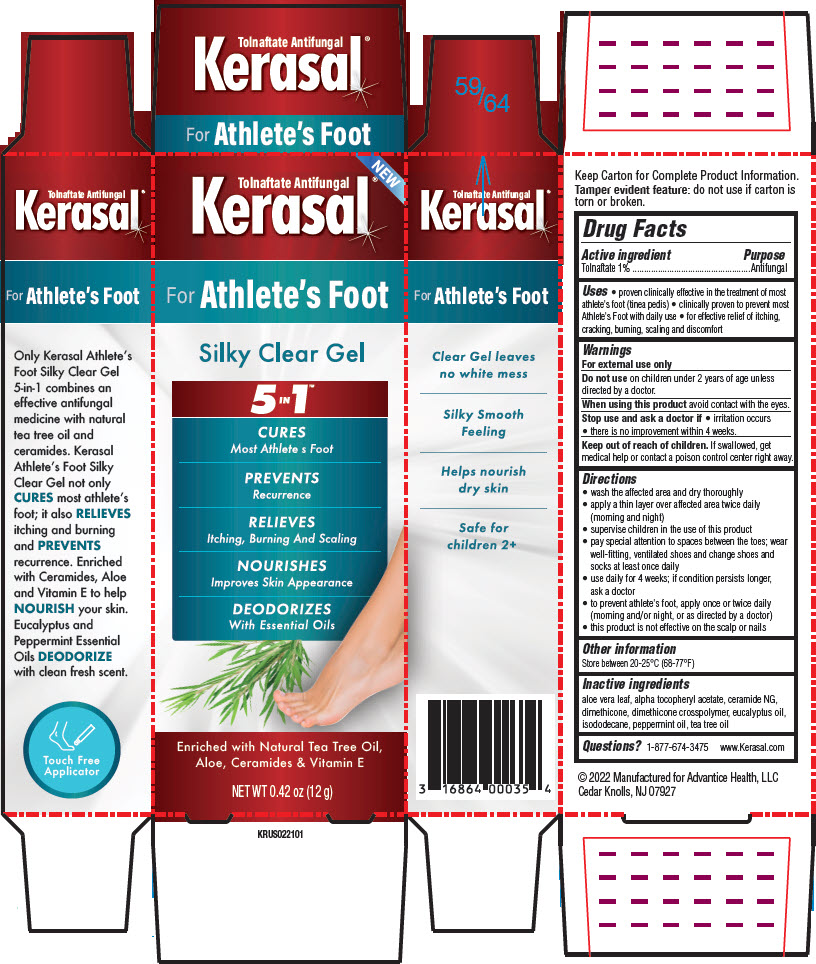 DRUG LABEL: Kerasal for Athletes Foot Silky Clear
NDC: 16864-100 | Form: GEL
Manufacturer: Advantice Health, LLC
Category: otc | Type: HUMAN OTC DRUG LABEL
Date: 20260113

ACTIVE INGREDIENTS: TOLNAFTATE 1 g/100 g
INACTIVE INGREDIENTS: ALOE VERA LEAF; .ALPHA.-TOCOPHEROL ACETATE; CERAMIDE NG; DIMETHICONE; DIMETHICONE CROSSPOLYMER (450000 MPA.S AT 12% IN CYCLOPENTASILOXANE); EUCALYPTUS OIL; ISODODECANE; PEPPERMINT OIL; TEA TREE OIL

Kerasal®for Athlete's Foot Silky Clear Gel

Drug Facts

Active ingredient

Tolnaftate 1%

Purpose

Antifungal

Uses

- proven clinically effective in the treatment of most athlete's foot (tinea pedis)
- clinically proven to prevent most Athlete's Foot with daily use
- for effective relief of itching, cracking, burning, scaling and discomfort

Warnings

For external use only

DO NOT USE

Do not useon children under 2 years of age unless directed by a doctor.

When using this productavoid contact with the eyes.

Stop use and ask a doctor if

- irritation occurs
- there is no improvement within 4 weeks.

Keep out of reach of children.If swallowed, get medical help or contact a poison control center right away.

Directions

- wash the affected area and dry thoroughly
- apply a thin layer over affected area twice daily (morning and night)
- supervise children in the use of this product
- pay special attention to spaces between the toes; wear well-fitting, ventilated shoes and change shoes and socks at least once daily
- use daily for 4 weeks; if condition persists longer, ask a doctor
- to prevent athlete's foot, apply once or twice daily (morning and/or night, or as directed by a doctor)
- this product is not effective on the scalp or nails

Other information

Store between 20-25°C (68-77°F)

Inactive ingredients

aloe vera leaf, alpha tocopheryl acetate, ceramide NG, dimethicone, dimethicone crosspolymer, eucalyptus oil, isododecane, peppermint oil, tea tree oil

Questions?

1-877-674-3475
www.Kerasal.com

PRINCIPAL DISPLAY PANEL - 12 g Tube Carton

NEW

Tolnaftate Antifungal
Kerasal®

For Athlete's Foot

Silky Clear Gel

5 IN 1™

CURES
Most Athlete s Foot

PREVENTS
Recurrence

RELIEVES
Itching, Burning And Scaling

NOURISHES
Improves Skin Appearance

DEODORIZES
With Essential Oils

Enriched with Natural Tea Tree Oil,
Aloe, Ceramides & Vitamin E

NET WT 0.42 oz (12 g)